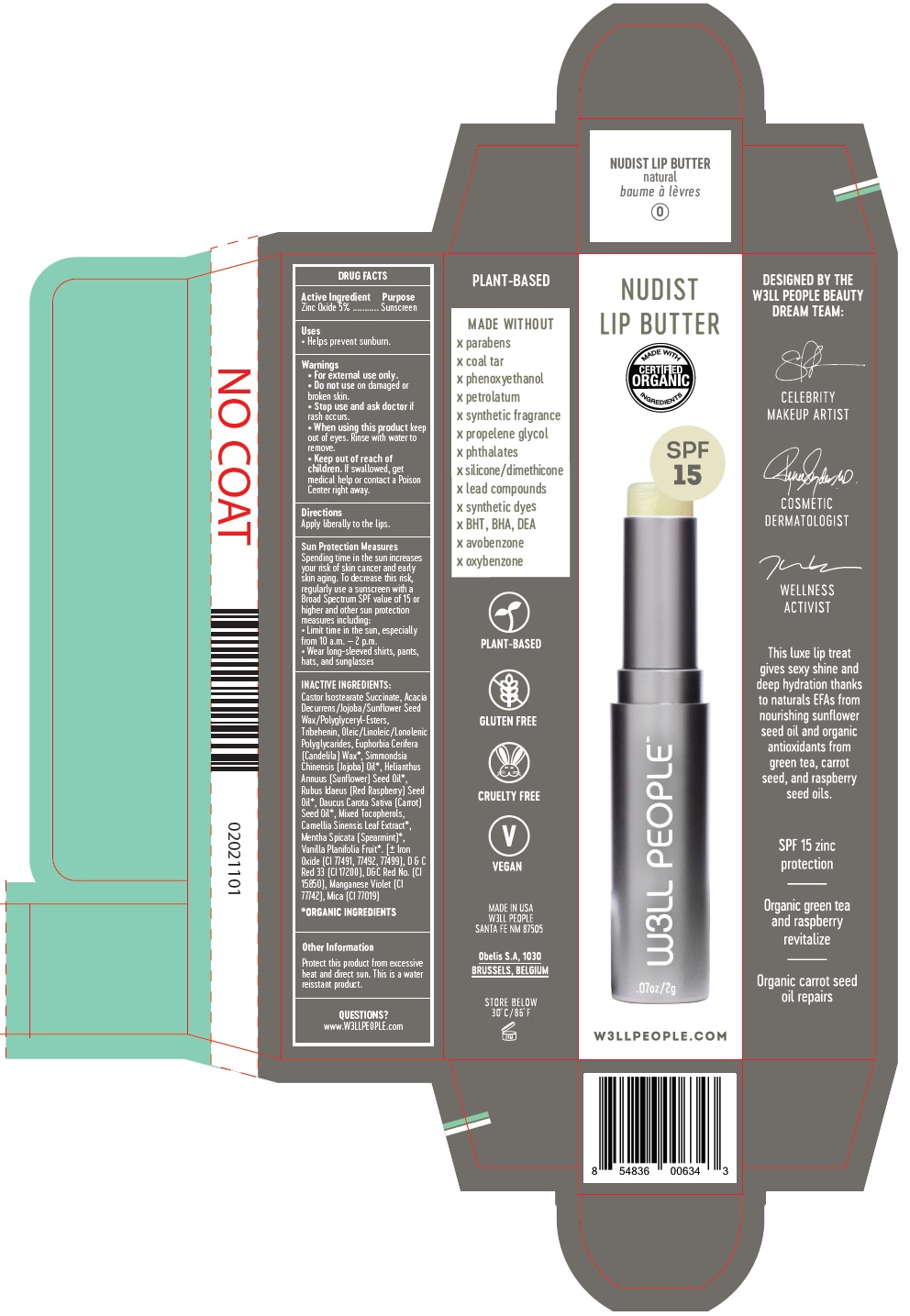 DRUG LABEL: NUDIST LIP BUTTER natural
NDC: 73621-001 | Form: STICK
Manufacturer: W3LL PEOPLE INC
Category: otc | Type: HUMAN OTC DRUG LABEL
Date: 20200623

ACTIVE INGREDIENTS: ZINC OXIDE 5 g/100 g
INACTIVE INGREDIENTS: ACACIA DECURRENS FLOWER; TRIBEHENIN; JOJOBA OIL; CANDELILLA WAX; LINOLEIC ACID; ISOSTEARIC ACID; SUCCINIC ACID; CASTOR OIL; SUNFLOWER OIL; RASPBERRY SEED OIL; CARROT SEED OIL; TOCOPHEROL; GREEN TEA LEAF; MENTHA SPICATA OIL; VANILLA BEAN

Active Ingredient

Zinc Oxide 5%

Purpose

Sunscreen

Uses

• Helps prevent sunburn.

Warnings

- For external use only.
- Do not use on damaged or broken skin.
- Stop use and ask doctor if skin rash occurs.
- When using this product keep out of eyes. Rinse with water to remove.
- Keep out of reach of children. If swallowed, get medical help or contact Poison Control Center right away.

Directions

Apply liberally to the lips.

Sun Protection Measures

Spending time in the sun increases your risk of skin cancer and early skin aging. To decrease this risk, regularly use a sunscreen with a Broad

Spectrum SPF value of 15 or higher and other sun protection measures including:

• Limit time in the sun, especially from 10 a.m. – 2 p.m.

• Wear long-sleeved shirts, pants, hats, and sunglasses

Inactive Ingredients

Castor Isostearate Succinate, Acacia Decurrens/Jojoba/Sunflower Seed Wax/Polyglyceryl-Esters, Tribehenin, Oleic/Linoleic/Lonolenic
Polyglycarides, Euphorbia Cerifera (Candelila) Wax*, Simmondsia Chinensis (Jojoba) Oil*, Helianthus Annuus (Sunflower) Seed Oil*,
Rubus Idaeus (Red Raspberry) Seed Oil*, Daucus Carota Sativa (Carrot) Seed Oil*, Mixed Tocopherols, Camellia Sinensis Leaf Extract*,
Mentha Spicata (Spearmint)*, Vanilla Planifolia Fruit*. [± Iron Oxide (CI 77491, 77492, 77499), D & C Red 33 (CI 17200), D&C Red No. (CI
15850), Manganese Violet (CI 77742), Mica (CI 77019)

*ORGANIC INGREDIENTS

Other Information

Protect this product from excessive heat and direct sun. This is a water reisstant product.

Questions?

www.W3LLPEOPLE.com